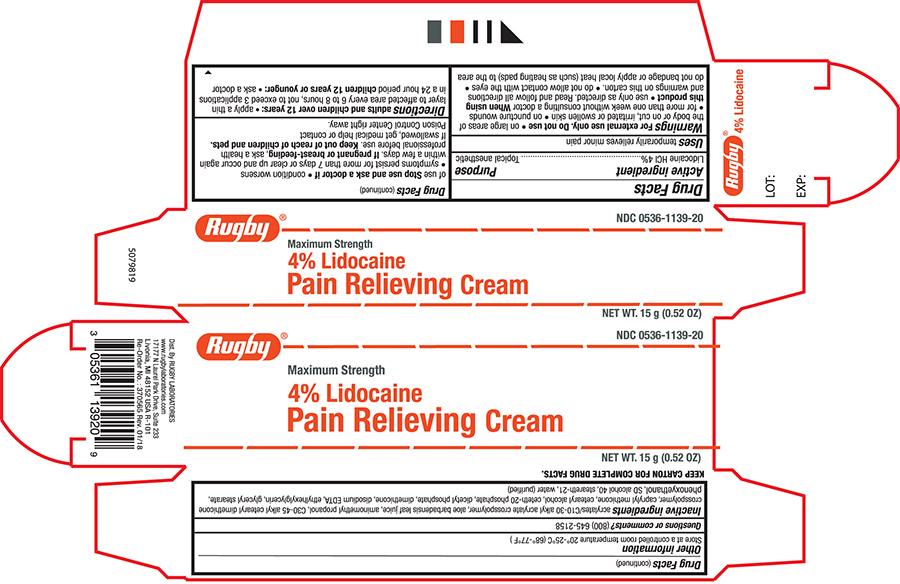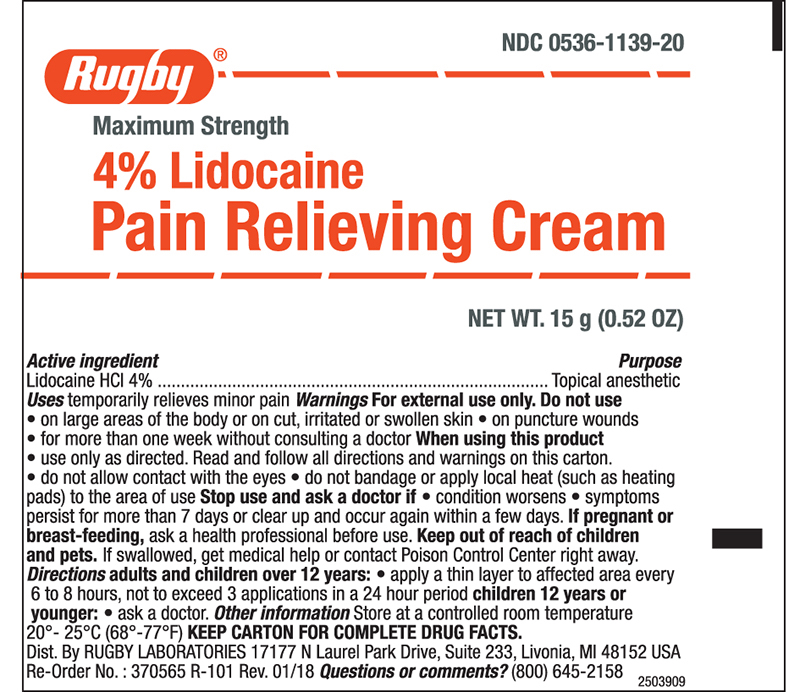 DRUG LABEL: Rugby Lidocaine
NDC: 0536-1139 | Form: CREAM
Manufacturer: Rugby Laboratories
Category: otc | Type: HUMAN OTC DRUG LABEL
Date: 20251124

ACTIVE INGREDIENTS: LIDOCAINE HYDROCHLORIDE 40 mg/1 g
INACTIVE INGREDIENTS: WATER; SILICON; ALCOHOL; CARBOMER INTERPOLYMER TYPE B (ALLYL PENTAERYTHRITOL CROSSLINKED); DIMETHICONE 350; AMINOMETHYLPROPANOL; ETHYLHEXYLGLYCERIN; PHENOXYETHANOL; STEARETH-21; GLYCERYL MONOSTEARATE; EDETATE DISODIUM ANHYDROUS; ALOE VERA LEAF; CETEARETH-2 PHOSPHATE

Drug Facts

Active ingredient

Lidocaine HCL 4%

Purpose

Topical anesthetic

Uses

- Temporarily relieves minor pain

Warnings

For external use only

Do not use

- on large areas of the body or on cut,irritated or swollen skin
- on puncture wounds
- for more than one week without consultanting a doctor

When using this product

use only as directed. read and follow all directions and warnings on this carton.

do notallow contact with the eyes

do not bandage or apply local heat (such as heating pads) to the area of use.

Stop use and ask a doctor if

- condition worsens
- symptons persist for more than 7 days or clear up and occur again within a few days.
- If pregnant or breast feeding, ask a health professional before use.

Keep this and all drugs out of the reach of children and pets.

If swallowed, get medical help or contact Poison Control Center right away.

Directions

- Adults and children over 12 years:
- apply a thin layer ot affected area every 6 t o8 hours, not to exceed 3 applications in a 24 hour period
- Children under 12 years or younger:ask a doctor

Other information

- Store at controlled room temperature 20°-25°C (68°-77°F)

Inactive ingredients

Acrylates/C10-30 Alkyl Acrylate Crosspolymer, Aloe Barbadensis Leaf Juice, Aminomethyl Propanol, C30-45 Alkyl Cetearyl Dimethicone Crosspolymer, Caprylyl Methicone, Cetearyl Alcohol, Ceteth-20 Phosphate, Dicetyl Phosphate, Dimethicone, Disodium EDTA, Ethylhexylglycerin, Glyceryl Stearate, Phenoxyethanol, SD Alcohol 40, Steareth-21, Water (purified)

Principal Panel-Tube

RUGBY® NDC 0536-1139-20

Maxium Strength

4% Lidocaine

Pain Relieving Cream

NET WT. 15g (0.52 oz)

Principal Panel - Carton

RUGBY® NDC 0536-1139-20

Maxium Strength

4% Lidocaine

Pain Relieving Cream

NET WT. 15g (0.52 oz)